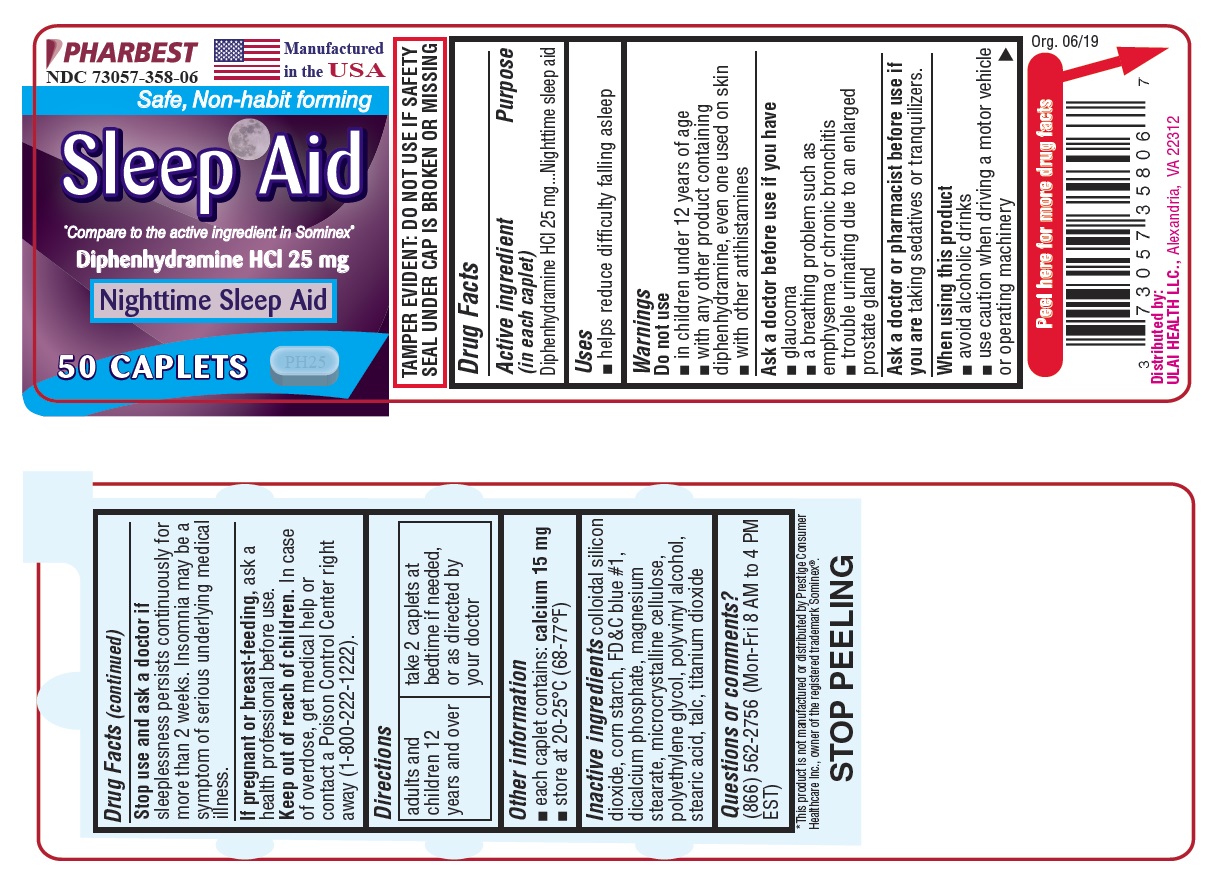 DRUG LABEL: Sleep Aid
NDC: 73057-358 | Form: TABLET
Manufacturer: Ulai Health LLC
Category: otc | Type: HUMAN OTC DRUG LABEL
Date: 20220131

ACTIVE INGREDIENTS: DIPHENHYDRAMINE HYDROCHLORIDE 25 mg/1 1
INACTIVE INGREDIENTS: SILICON DIOXIDE; STARCH, CORN; FD&C BLUE NO. 1; CALCIUM PHOSPHATE, DIBASIC, ANHYDROUS; MAGNESIUM STEARATE; CELLULOSE, MICROCRYSTALLINE; POLYETHYLENE GLYCOL, UNSPECIFIED; POLYVINYL ALCOHOL, UNSPECIFIED; STEARIC ACID; TALC; TITANIUM DIOXIDE

Drug Facts

Active ingredient (in each caplet)

Diphenhydramine HCl 25 mg

Purpose

Nighttime sleep aid

Uses

- helps reduce difficulty falling asleep

Do not use

- in children under 12 years of age
- with any other product containing diphenhydramine, even one used on skin
- with other antihistamines

Ask a doctor before use if you have

- glaucoma
- a breathing problem such as emphysema or chronic bronchitis
- trouble urinating due to an enlarged prostate gland

Ask a doctor or pharmacist before use if you are

taking sedatives or tranquilizers.

When using this product

- avoid alcoholic drinks
- use caution when driving a motor vehicle or operating machinery

Stop use and ask a doctor if

sleeplessness persists continuously for more than 2 weeks. Insomnia may be a symptom of serious underlying medical illness.

If pregnant or breast-feeding,

ask a health professional before use.

Keep out of reach of children.

In case of overdose, get medical help or contact a Poison Control Center right away (1-800-222-1222).

Directions

adults and children 12 years and over | take 2 caplets at bedtime if needed, or as directed by your doctor

Other information

- each caplet contains: calcium 15 mg
- store at 20-25oC (68-77oF)

Inactive ingredients

colloidal silicon dioxide, corn startch, FD&C blue #1, dicalcium phosphate, magnesium stearate, microcrystalline cellulose, polyethylene glycol, polyvinyl alcohol, stearic acid, talc, titanium dioxide

Questions or comments?

(866) 562-2756 (Mon-Fri 8 AM to 4 PM EST)

PACKAGE LABEL

PHARBEST

NDC 73057-358-06

Manufactured in the USA

Safe, Non-habit forming

Sleep Aid

*Compare to the active ingredient in Sominex®

Diphenhydramine HCl 25 mg

Nighttime Sleep Aid

50 CAPLETS